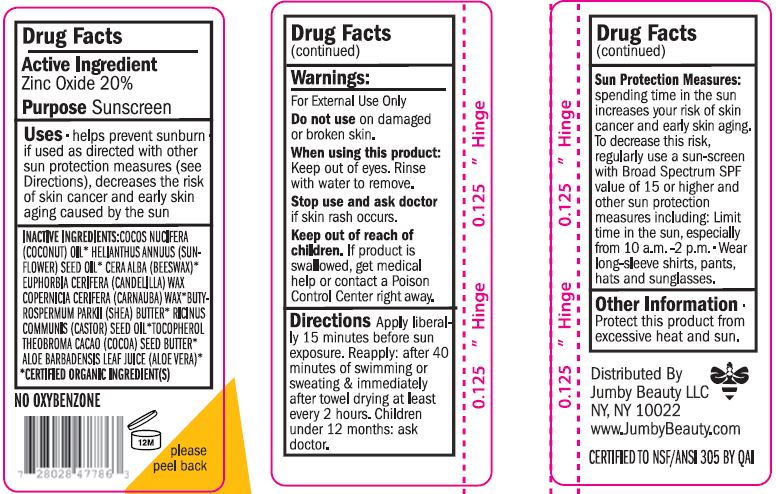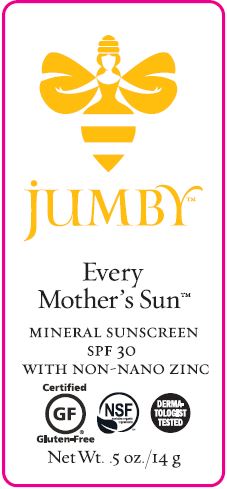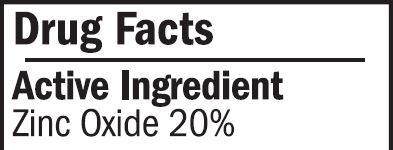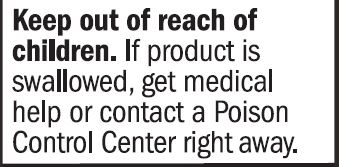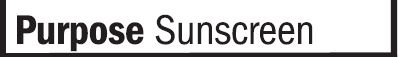 DRUG LABEL: Sunscreen
NDC: 62932-234 | Form: STICK
Manufacturer: Private Label Select Ltd CO
Category: otc | Type: HUMAN OTC DRUG LABEL
Date: 20201229

ACTIVE INGREDIENTS: ZINC OXIDE 20 g/100 g
INACTIVE INGREDIENTS: SUNFLOWER OIL; .ALPHA.-TOCOPHEROL, D-; COCONUT OIL; ALOE VERA LEAF; .GAMMA.-TOCOPHEROL; .DELTA.-TOCOPHEROL; WHITE WAX; CANDELILLA WAX; SHEA BUTTER; COCOA BUTTER; CASTOR OIL; .BETA.-TOCOPHEROL; CARNAUBA WAX

Jumby Every Mother's Sun, Mineral Sunscreen SPF 30 (Stick)